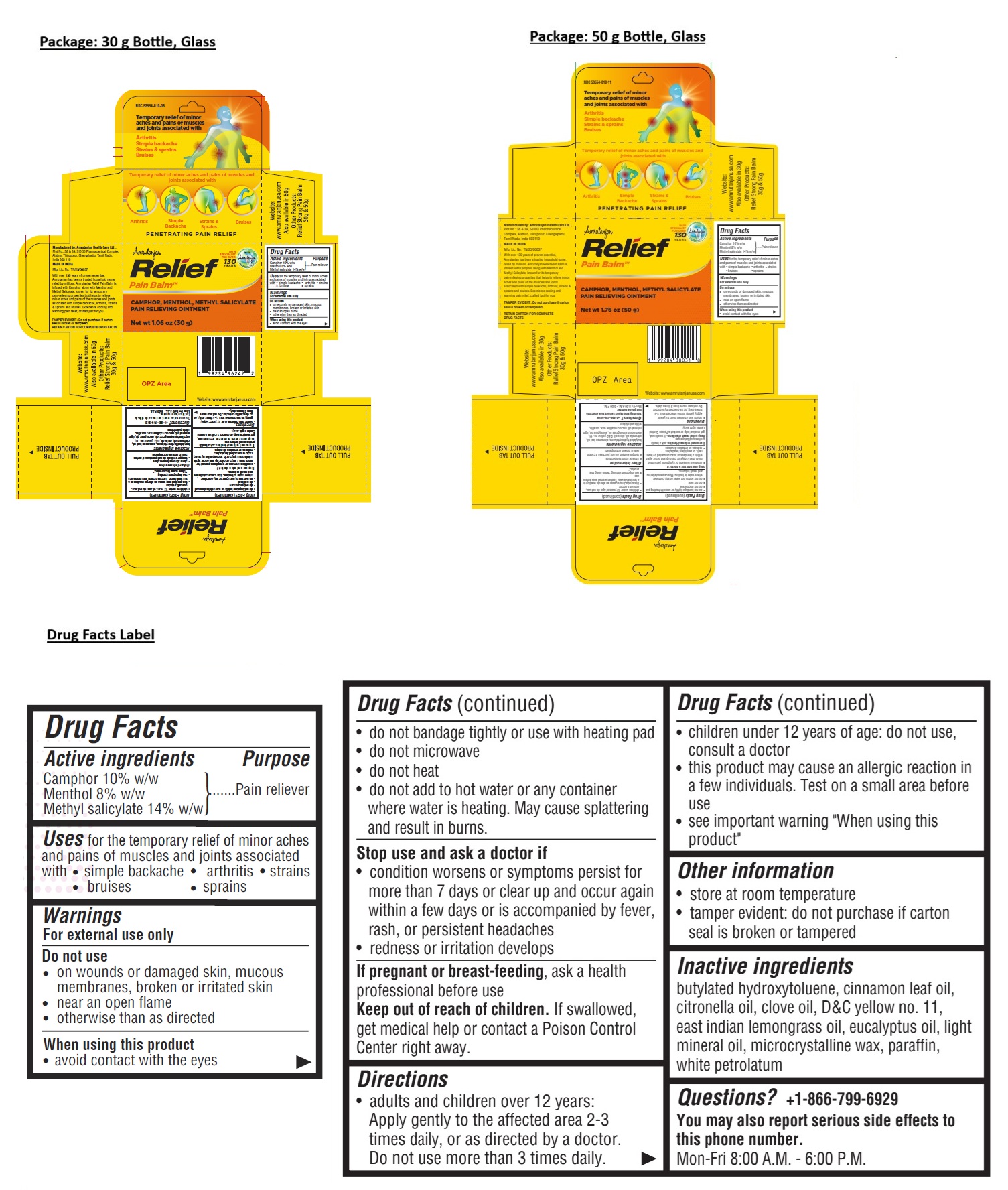 DRUG LABEL: AMRUTANJAN RELIEF PAIN BALM
NDC: 53554-010 | Form: OINTMENT
Manufacturer: AMRUTANJAN HEALTH CARE LIMITED
Category: otc | Type: HUMAN OTC DRUG LABEL
Date: 20250723

ACTIVE INGREDIENTS: CAMPHOR (SYNTHETIC) 0.1 g/1 g; MENTHOL, UNSPECIFIED FORM 0.08 g/1 g; METHYL SALICYLATE 0.14 g/1 g
INACTIVE INGREDIENTS: BUTYLATED HYDROXYTOLUENE; CINNAMON LEAF OIL; CITRONELLA OIL; CLOVE OIL; D&C YELLOW NO. 11; EAST INDIAN LEMONGRASS OIL; EUCALYPTUS OIL; LIGHT MINERAL OIL; MICROCRYSTALLINE WAX; PARAFFIN; WHITE PETROLATUM

Amrutanjan Relief Pain Balm™

Active ingredients

Camphor 10% w/w
Menthol 8% w/w
Methyl salicylate 14% w/w

Purpose

Pain reliever

Uses

for the temporary relief of minor aches and pains of muscles and joints associated with • simple backache • arthritis • strains • bruises • sprains

Warnings

For external use only

Do not use
• on wounds or damaged skin, mucous membranes, broken or irritated skin
• near an open flame
• otherwise than as directed

When using this product
• avoid contact with the eyes
• do not bandage tightly or use with heating pad
• do not microwave
• do not heat
• do not add to hot water or any container where water is heating. May cause splattering and result in burns.

Stop use and ask a doctor if
• condition worsens or symptoms persist for more than 7 days or clear up and occur again within a few days or is accompanied by fever, rash, or persistent headaches
• redness or irritation develops

If pregnant or breast-feeding, ask a health professional before use

Keep out of reach of children. If swallowed, get medical help or contact a Poison Control Center right away.

Directions

• adults and children over 12 years: Apply gently to the affected area 2-3 times daily, or as directed by a doctor. Do not use more than 3 times daily.
• children under 12 years of age: do not use, consult a doctor
• this product may cause an allergic reaction in a few individuals. Test on a small area before use
• see important warning "When using this product"

Other information

• store at room temperature
• tamper evident: do not purchase if carton seal is broken or tampered

Inactive ingredients

butylated hydroxytoluene, cinnamon leaf oil, citronella oil, clove oil, D&C yellow no. 11, east indian lemongrass oil, eucalyptus oil, light mineral oil, microcrystalline wax, paraffin, white petrolatum

Questions?

+1-866-799-6929
You may also report serious side effects to this phone number.
Mon-Fri 8:00 A.M. - 6:00 P.M.

PAIN SPECIALIST FOR OVER 130 YEARS

Since 1983
Pure Healthy Essence

Manufactured by: Amrutanjan Health Care Ltd.,
Plot No.: 38 & 39, SIDCO Pharmaceutical Complex,
Alathur, Thiruporur, Chengalpattu,
Tamil Nadu, India 603110

MADE IN INDIA

Mfg. Lic. No. TN/25/00037

With over 130 years of proven expertise, Amrutanjan has been a trusted household name, relied by millions. Amrutanjan Relief Pain Balm is infused with Camphor along with Menthol and Methyl Salicylate, known for its temporary pain-relieving properties that helps to relieve minor aches and pains of the muscles and joints associated with simple backache, arthritis, strains & sprains and bruises. Experience cooling and warming pain relief, crafted just for you.

TAMPER EVIDENT: Do not purchase if carton seal is broken or tampered.

RETAIN CARTON FOR COMPLETE DRUG FACTS

PENETRATING PAIN RELIEF

Website:
www.amrutanjanusa.com

Other Products:
Relief Strong Pain Balm
30g & 50g